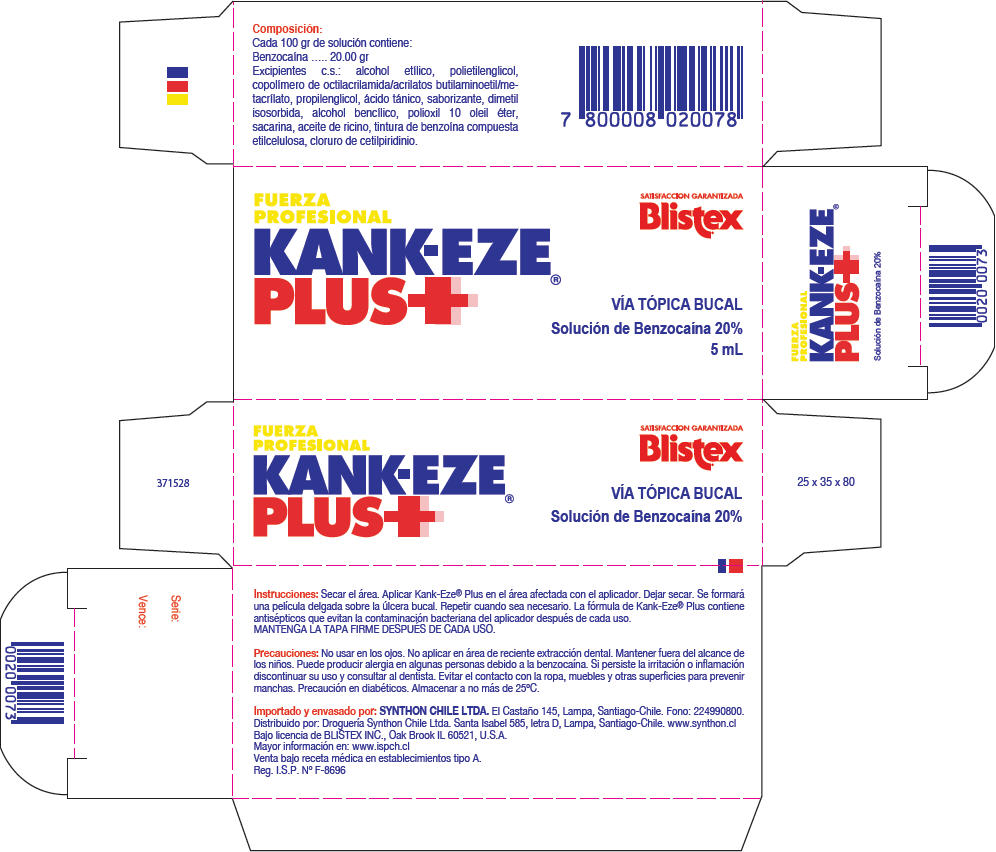 DRUG LABEL: Blistex Kank-Eze
NDC: 10157-9411 | Form: GEL
Manufacturer: Blistex Inc.
Category: otc | Type: HUMAN OTC DRUG LABEL
Date: 20160606

ACTIVE INGREDIENTS: BENZOCAINE 20 g/100 mL
INACTIVE INGREDIENTS: POLYETHYLENE GLYCOL 300; TANNIC ACID; DIMETHYL ISOSORBIDE; BENZYL ALCOHOL; CASTOR OIL; ETHYLCELLULOSES; CETYLPYRIDINIUM CHLORIDE; SACCHARIN; ALCOHOL; Propylene Glycol; Oleth-10; Benzoin Resin

Blistex® Kank-Eze®